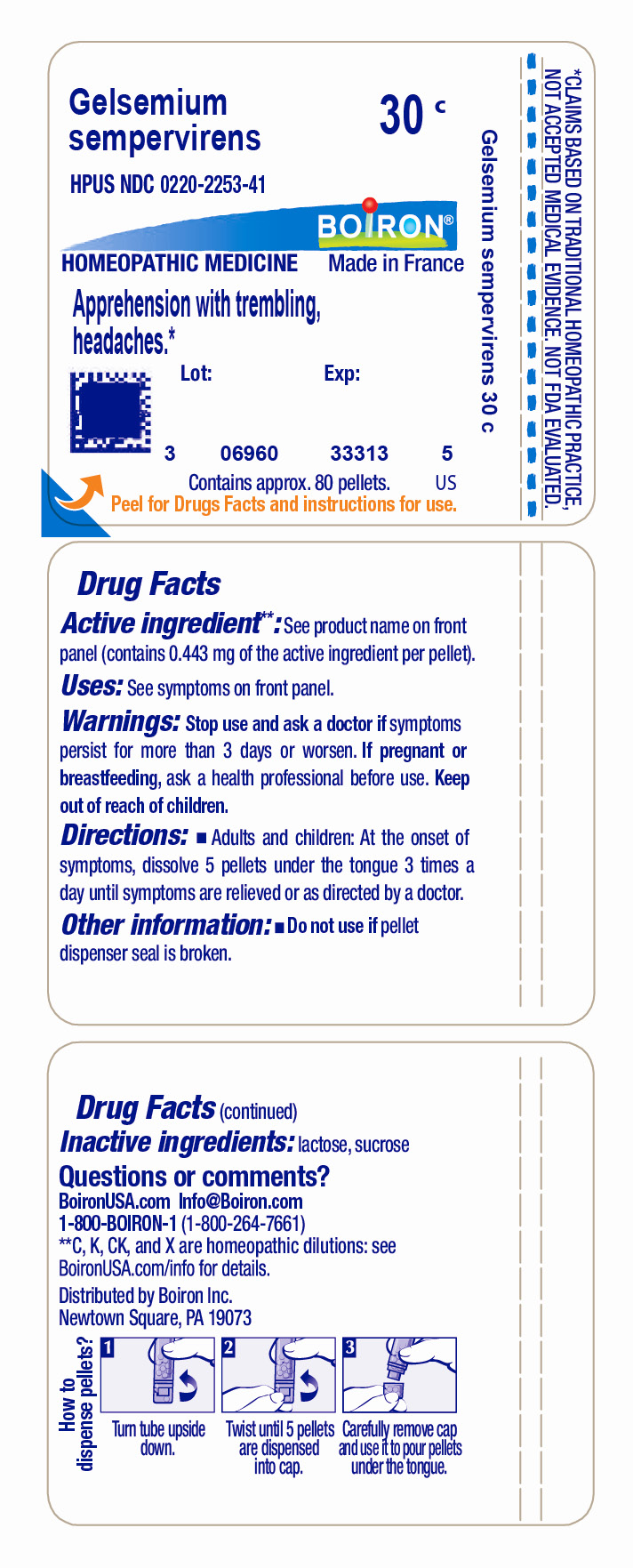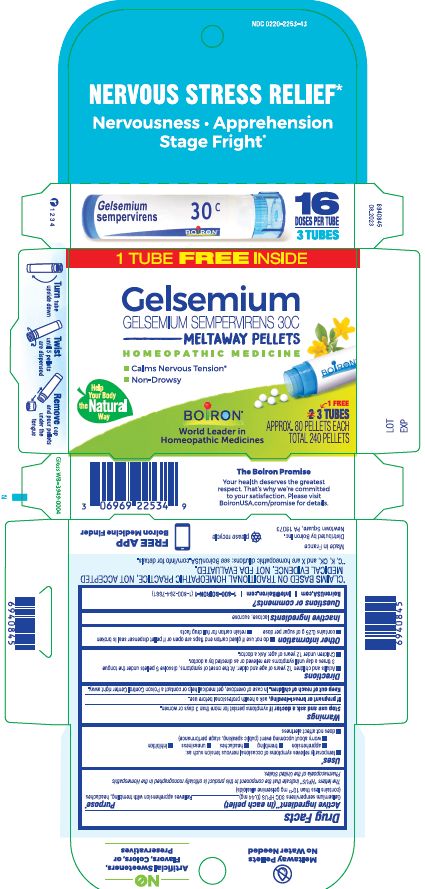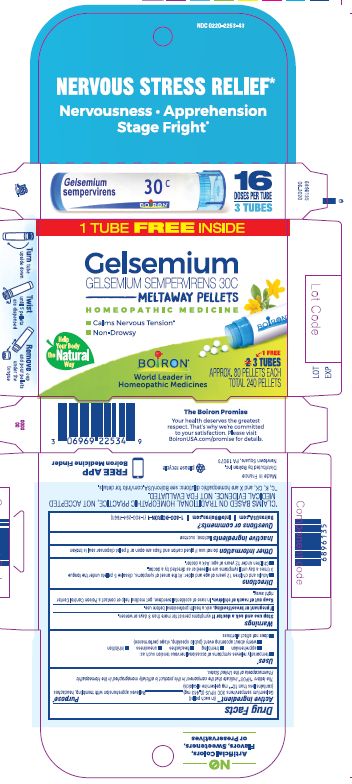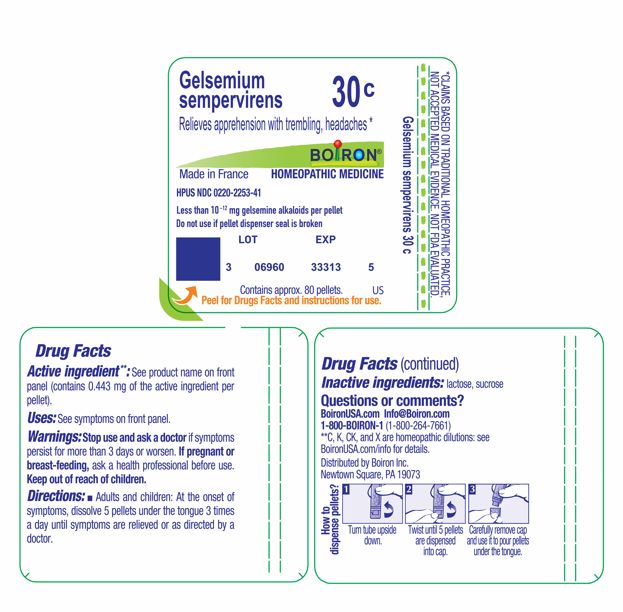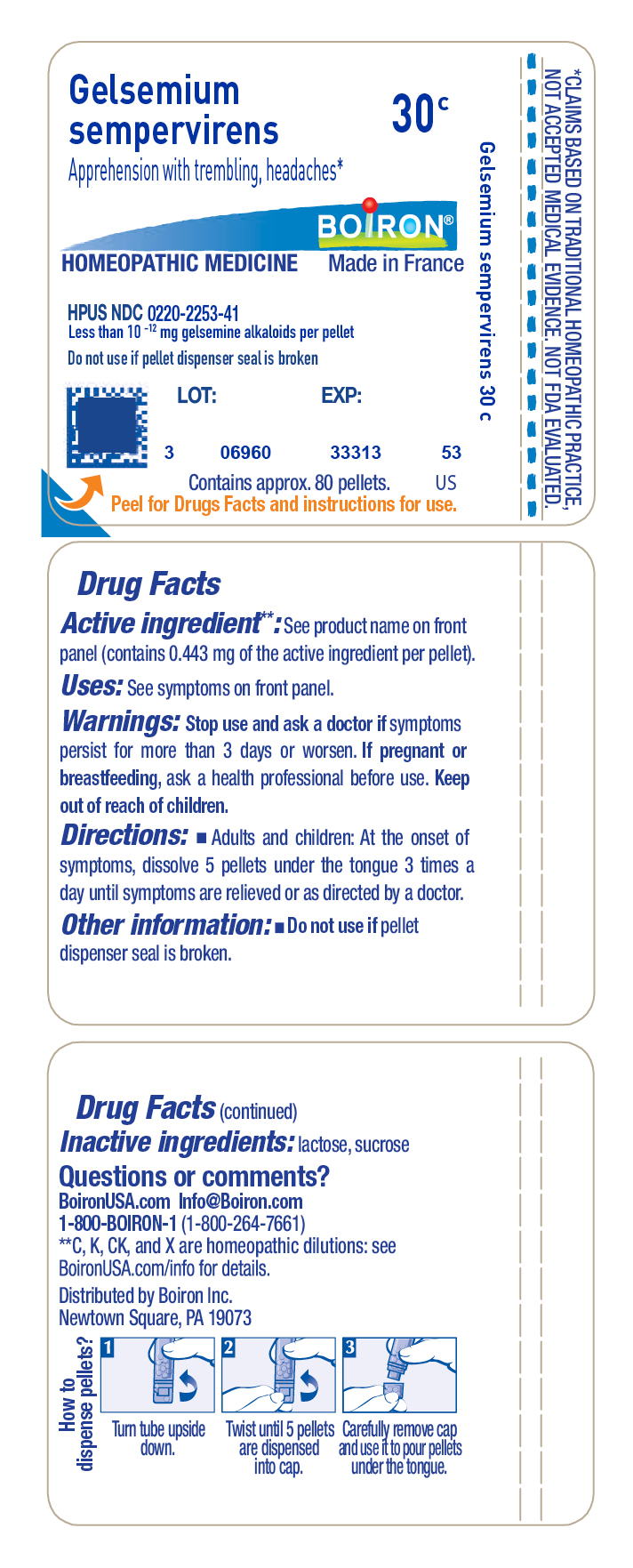 DRUG LABEL: Gelsemium sempervirens
NDC: 0220-2253 | Form: PELLET
Manufacturer: Boiron
Category: homeopathic | Type: HUMAN OTC DRUG LABEL
Date: 20251024

ACTIVE INGREDIENTS: GELSEMIUM SEMPERVIRENS ROOT 30 [hp_C]/30 [hp_C]
INACTIVE INGREDIENTS: SUCROSE; LACTOSE, UNSPECIFIED FORM

Gelsemium sempervirens 30C

Active ingredient**

Gelsemium sempervirens 30C HPUS (0.44 mg)

(contains less than 10^-12 mg gelsemine alkaloids per pellet)

The letters "HPUS" indicate that the component in this product are officially monographed in the Homeopathic Pharmacopoeia of the United States.

Purpose*

Gelsemium sempervirens 30C HPUS (0.44 mg) ... Relieves apprehension with trembling, headaches

Uses*

- temporarily relieves symptoms of occasional nervous tension such as:
- apprehension
- trembling
- headaches
- uneasiness
- inhibition
- worry about upcoming event (public speaking, stage performance)
- does not affect alertness

Stop use and ask a doctor if symptoms persist for more than 3 days or worsen.

PREGNANCY OR BREAST FEEDING

If pregnant or breast-feeding, ask a health professional before use.

Keep out of reach of children. In case of overdose, get medical help or contact a Poison Control Center right away.

DOSAGE AND ADMINISTRATION

Tube - Adults and children: At the onset of symptoms, dissolve 5 pellets under the tongue 3 times a day until symptoms are relieved or as directed by a doctor.

Box - Adults and children 12 years of age and older: At the onset of symptoms, dissolve 5 pellets under the tongue 3 times a day until symptoms are relieved or as directed by a doctor. Children under 12 years of age: Ask a doctor.

INACTIVE INGREDIENT

lactose, sucrose

QUESTIONS

BoironUSA.com Info@boiron.com
1-800-BOIRON-1 (1-800-264-7661)
Distributed by Boiron, Inc.
Newtown Square, PA 19073

Do not use if glued carton end flaps are open or if pellet dispenser seal is broken.

Do not use if pellet dispenser seal is broken.

contains 0.25g of sugar per dose

retain carton for full drug facts

3 TUBES

APPROX. 80 PELLETS EACH

TOTAL 240 PELLETS

NERVOUS STRESS RELIEF*

Nervousness Apprehension Stage Fright*

How to dispense pellets? Turn tube upside down. Twist until 5 pellets are dispensed. Remove cap and pour pellets under the tongue.

*CLAIMS BASED ON TRADITIONAL HOMEOPATHIC PRACTICE NOT ACCEPTED MEDICAL EVIDENCE. NOT FDA EVALUATED.

*C,K,CK, and X are homeopathic dilutions: see BoironUSA.com/info for details.